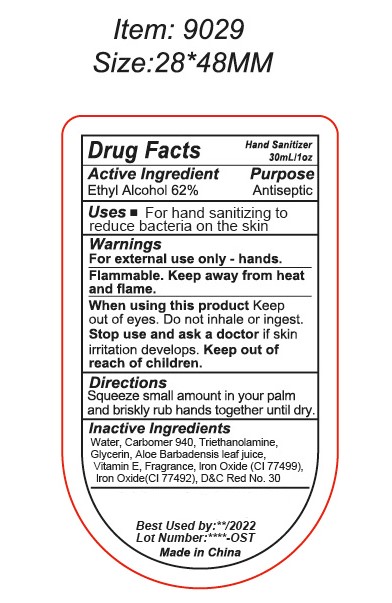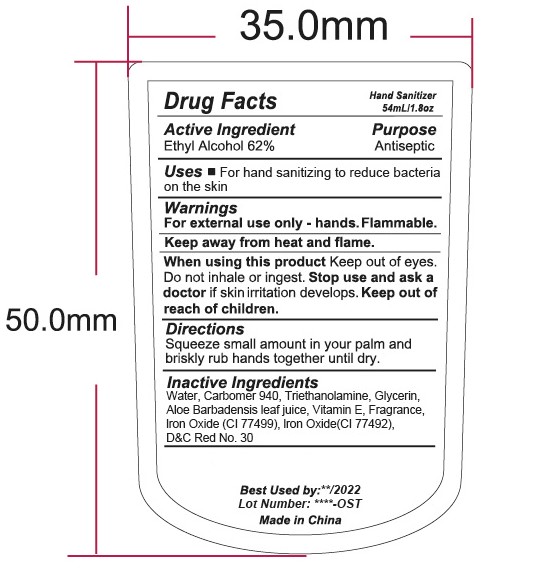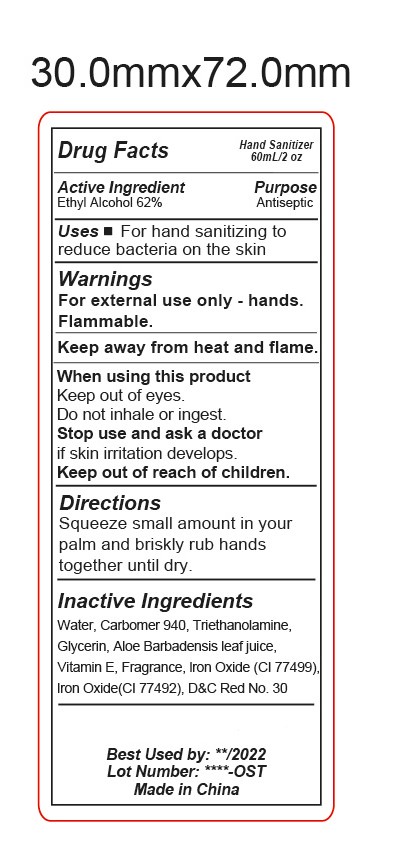 DRUG LABEL: HAND SANITIZER
NDC: 47993-299 | Form: GEL
Manufacturer: NINGBO JIANGBEI OCEAN STAR TRADING CO.,LTD
Category: otc | Type: HUMAN OTC DRUG LABEL
Date: 20201105

ACTIVE INGREDIENTS: ALCOHOL 62 g/112 mL
INACTIVE INGREDIENTS: WATER; CARBOMER 940; TRIETHANOLAMINE BENZOATE; GLYCERIN; ALOE VERA LEAF; TOCOPHEROL; FERROSOFERRIC OXIDE; FERRIC OXIDE YELLOW; D&C RED NO. 30

47993-299

Active ingredients

Ethyl Alcohol 62%

PURPOSE

Antiseptic

Uses：

For hand sanitizing to reduce bacteria on the skin.

Warnings:

For external use only - hands.

Flammable. Keep away from fire and flame.

When using this product Keep out of reach of eyes. Do not inhale or ingest.

Stop use and ask a doctor if skin irritation develops.

Keep out of reach of children.

Directions:

Squeeze small amount in your palm and briskly rub hands together until dry.

Inactive Ingredients:

Water,Carbomer 940,Triethanolamine,Glycerin,Aloe Barbadensis leaf juice,Vitamin E,Fragrance,Iron Oxide(CI 77499),Iron Oxide(CI 77492),D&C Red No.30